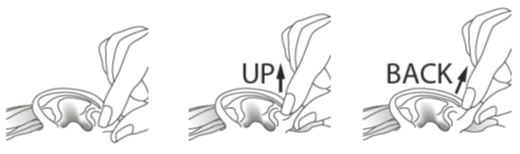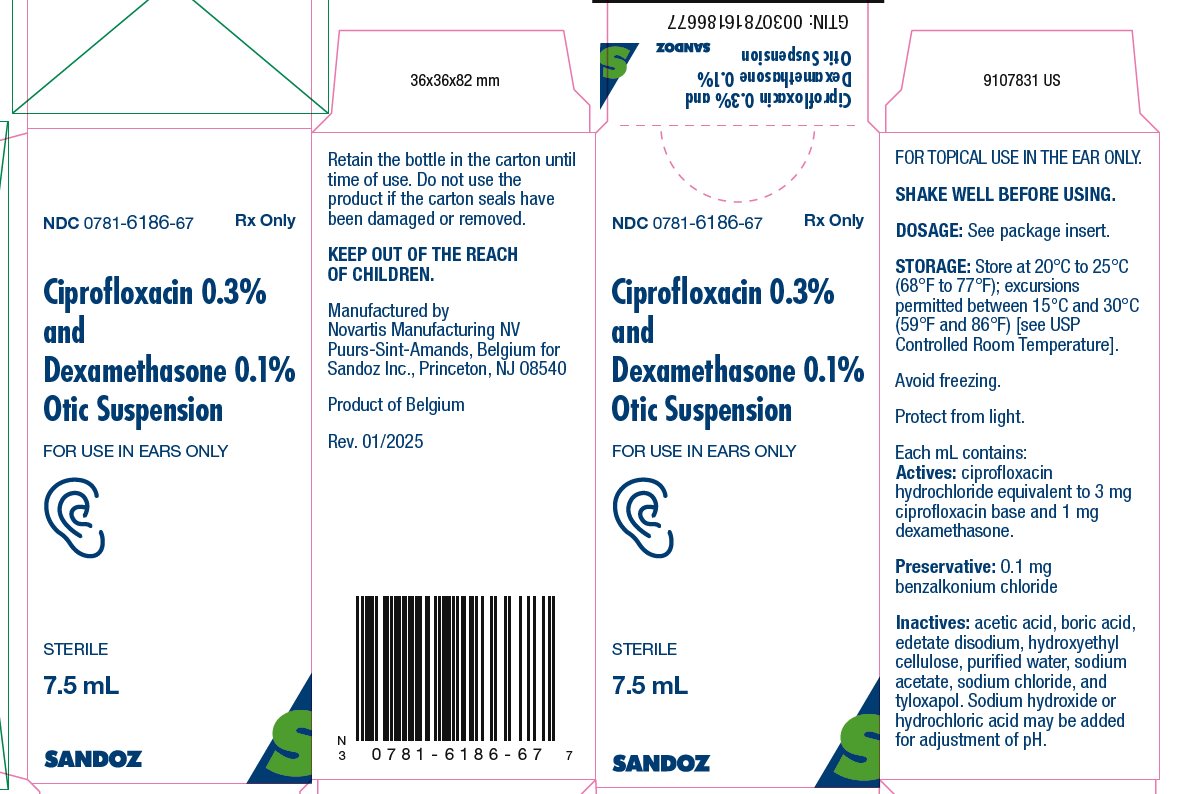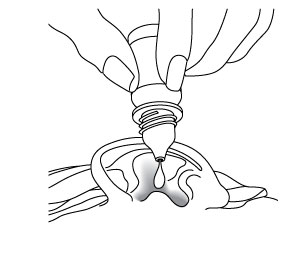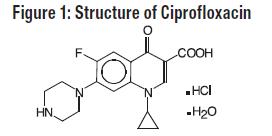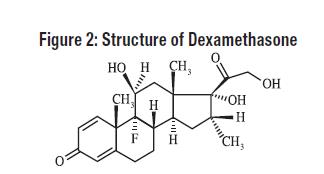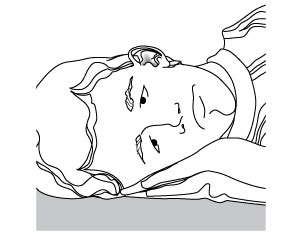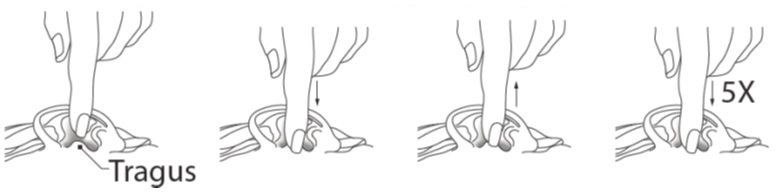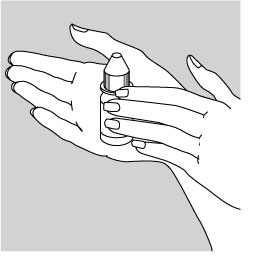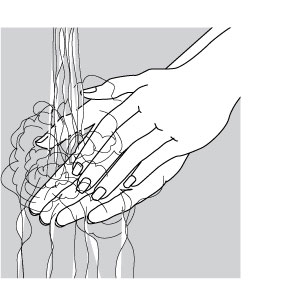 DRUG LABEL: Ciprofloxacin and Dexamethasone
NDC: 0781-6186 | Form: SUSPENSION/ DROPS
Manufacturer: Sandoz Inc
Category: prescription | Type: HUMAN PRESCRIPTION DRUG LABEL
Date: 20250131

ACTIVE INGREDIENTS: CIPROFLOXACIN HYDROCHLORIDE 3 mg/1 mL; Dexamethasone 1 mg/1 mL
INACTIVE INGREDIENTS: Benzalkonium Chloride; Boric Acid; Sodium Chloride; Hydroxyethyl Cellulose (1500 Mpa.s At 1%); Tyloxapol; Acetic Acid; Sodium Acetate; Edetate Disodium; Water; Sodium Hydroxide; Hydrochloric Acid

HIGHLIGHTS OF PRESCRIBING INFORMATION

These highlights do not include all the information needed to use CIPROFLOXACIN AND DEXAMETHASONE OTIC SUSPENSION safely and effectively. See full prescribing information for CIPROFLOXACIN AND DEXAMETHASONE OTIC SUSPENSION.
CIPROFLOXACIN AND DEXAMETHASONE otic suspension
Initial U.S. Approval: 2003

1 INDICATIONS AND USAGE

Ciprofloxacin and dexamethasone otic suspension is a combination of ciprofloxacin, a fluoroquinolone antibacterial and dexamethasone, a corticosteroid, indicated for the treatment of infections caused by susceptible isolates of the designated microorganisms in the specific conditions listed below:

- Acute Otitis Media (AOM) in pediatric patients (age 6 months and older) with tympanostomy tubes due to Staphylococcus aureus, Streptococcus pneumoniae, Haemophilus influenzae, Moraxella catarrhalis, and Pseudomonas aeruginosa. (1)
- Acute Otitis Externa (AOE) in pediatric (age 6 months and older), adult, and elderly patients due to Staphylococcus aureus and Pseudomonas aeruginosa. (1)

2 DOSAGE AND ADMINISTRATION

Ciprofloxacin and dexamethasone otic suspension is for otic use (ears) only, not for ophthalmic use, or for injection. (2.1)

- Shake well immediately before use. (2.1)
- Instill four drops into the affected ear twice daily, for seven days. (2.2)

3 DOSAGE FORMS AND STRENGTHS

Otic Suspension: Each mL of ciprofloxacin and dexamethasone otic suspension contains ciprofloxacin hydrochloride 0.3% (equivalent to 3 mg ciprofloxacin base) and dexamethasone 0.1% (equivalent to 1 mg dexamethasone). (3)

4 CONTRAINDICATIONS

- Ciprofloxacin and dexamethasone otic suspension is contraindicated in patients with a history of hypersensitivity to ciprofloxacin, to other quinolones, or to any of the components in this medication. (4)
- Use of this product is contraindicated in viral infections of the external canal, including herpes simplex infections and fungal otic infections. (4)

5 WARNINGS AND PRECAUTIONS

- Hypersensitivity and anaphylaxis have been reported with systemic use of quinolones. Discontinue use if this occurs with use of ciprofloxacin and dexamethasone otic suspension. (5.1)
- Prolonged use may result in overgrowth of non-susceptible bacteria and fungi. (5.2)

6 ADVERSE REACTIONS

Most common adverse reactions were ear discomfort (3%), ear pain (2.3%), and ear pruritus (1.5%). (6)

To report SUSPECTED ADVERSE REACTIONS, contact Sandoz Inc., at 1-800-525-8747 or FDA at 1-800-FDA-1088 or www.fda.gov/medwatch.

FULL PRESCRIBING INFORMATION

1 INDICATIONS AND USAGE

Ciprofloxacin and dexamethasone otic suspension is indicated for the treatment of infections caused by susceptible isolates of the designated microorganisms in the specific conditions listed below:

- Acute Otitis Media (AOM) in pediatric patients (age 6 months and older) with tympanostomy tubes due to Staphylococcus aureus, Streptococcus pneumoniae, Haemophilus influenzae, Moraxella catarrhalis, and Pseudomonas aeruginosa.
- Acute Otitis Externa (AOE) in pediatric (age 6 months and older), adult and elderly patients due to Staphylococcus aureus and Pseudomonas aeruginosa.

2 DOSAGE AND ADMINISTRATION

2.1 Important Administration Instructions

- Ciprofloxacin and dexamethasone otic suspension is for otic use (ears) only, and not for ophthalmic use, or for injection.
- Shake well immediately before use.

2.2 Dosage

For the Treatment of Acute Otitis Media in Pediatric Patients (age 6 months and older) With Tympanostomy Tubes

The recommended dosage regimen through tympanostomy tubes is as follows:

- Four drops [equivalent to 0.14 mL of ciprofloxacin and dexamethasone otic suspension, (consisting of 0.42 mg of ciprofloxacin and 0.14 mg of dexamethasone)] instilled into the affected ear twice daily for seven days.
- The suspension should be warmed by holding the bottle in the hand for one or two minutes to avoid dizziness, which may result from the instillation of a cold suspension.
- The patient should lie with the affected ear upward, and then the drops should be instilled.
- The tragus should then be pumped 5 times by pushing inward to facilitate penetration of the drops into the middle ear.
- This position should be maintained for 60 seconds. Repeat, if necessary, for the opposite ear.
- Discard unused portion after therapy is completed.

For the Treatment of Acute Otitis Externa (age 6 months and older)

The recommended dosage regimen is as follows:

- Four drops [equivalent to 0.14 mL of ciprofloxacin and dexamethasone otic suspension, (consisting of 0.42 mg ciprofloxacin and 0.14 mg dexamethasone)] instilled into the affected ear twice daily for seven days.
- The suspension should be warmed by holding the bottle in the hand for one or two minutes to avoid dizziness, which may result from the instillation of a cold suspension.
- The patient should lie with the affected ear upward, and then the drops should be instilled.
- This position should be maintained for 60 seconds to facilitate penetration of the drops into the ear canal. Repeat, if necessary, for the opposite ear.
- Discard unused portion after therapy is completed.

3 DOSAGE FORMS AND STRENGTHS

Otic Suspension: Each mL of ciprofloxacin and dexamethasone otic suspension contains ciprofloxacin hydrochloride 0.3% (equivalent to 3 mg ciprofloxacin base) and dexamethasone 0.1% equivalent to 1 mg dexamethasone.

4 CONTRAINDICATIONS

- Ciprofloxacin and dexamethasone otic suspension is contraindicated in patients with a history of hypersensitivity to ciprofloxacin, to other quinolones, or to any of the components in this medication.
- Use of this product is contraindicated in viral infections of the external canal, including herpes simplex infections and fungal otic infections.

5 WARNINGS AND PRECAUTIONS

5.1 Hypersensitivity Reactions

Ciprofloxacin and dexamethasone otic suspension should be discontinued at the first appearance of a skin rash or any other sign of hypersensitivity. Serious and occasionally fatal hypersensitivity (anaphylactic) reactions, some following the first dose, have been reported in patients receiving systemic quinolones. Some reactions were accompanied by cardiovascular collapse, loss of consciousness, angioedema (including laryngeal, pharyngeal, or facial edema), airway obstruction, dyspnea, urticaria, and itching.

5.2 Potential for Microbial Overgrowth with Prolonged Use

Prolonged use of ciprofloxacin and dexamethasone otic suspension may result in overgrowth of non-susceptible bacteria and fungi. If the infection is not improved after one week of treatment, cultures should be obtained to guide further treatment. If such infections occur, discontinue use and institute alternative therapy.

5.3 Continued or Recurrent Otorrhea

If otorrhea persists after a full course of therapy, or if two or more episodes of otorrhea occur within six months, further evaluation is recommended to exclude an underlying condition, such as cholesteatoma, foreign body, or a tumor.

6 ADVERSE REACTIONS

The following serious adverse reactions are described elsewhere in the labeling:

- Hypersensitivity Reactions [see Warnings and Precautions (5.1)]
- Potential for Microbial Overgrowth with Prolonged Use [see Warnings and Precautions (5.2)]

6.1 Clinical Trials Experience

Because clinical trials are conducted under widely varying conditions, adverse reaction rates observed in the clinical trials of a drug cannot be directly compared to the rates in the clinical trials of another drug and may not reflect the rates observed in practice.

In Phases II and III clinical trials, a total of 937 patients were treated with ciprofloxacin and dexamethasone otic suspension. This included 400 patients with acute otitis media with tympanostomy tubes (AOMT) and 537 patients with AOE. The reported adverse reactions are listed below:

Acute Otitis Media in Pediatric Patients with Tympanostomy Tubes

The following adverse reactions occurred in 0.5% or more of the patients with non-intact tympanic membranes.

Adverse Reactions | Incidence (N = 400)
Ear discomfort | 3.0%
Ear pain | 2.3%
Ear precipitate (residue) | 0.5%
Irritability | 0.5%
Taste Perversion | 0.5%

The following adverse reactions were each reported in a single patient: tympanostomy tube blockage; ear pruritus; tinnitus; oral moniliasis; crying; dizziness; and erythema.

Acute Otitis Externa

The following adverse reactions occurred in 0.4% or more of the patients with intact tympanic membranes.

Adverse Reactions | Incidence (N = 537)
Ear pruritus | 1.5%
Ear debris | 0.6%
Superimposed ear infection | 0.6%
Ear congestion | 0.4%
Ear pain | 0.4%
Erythema | 0.4%

The following adverse reactions were each reported in a single patient: ear discomfort; decreased hearing; and ear disorder (tingling).

6.2 Postmarketing Experience

The following adverse reactions have been identified during post approval use of ciprofloxacin and dexamethasone otic suspension. Because these reactions are reported voluntarily from a population of unknown size, it is not always possible to reliably estimate their frequency or establish a causal relationship to drug exposure. These reactions include auricular swelling, headache, hypersensitivity, otorrhea, skin exfoliation, rash erythematous, and vomiting.

8 USE IN SPECIFIC POPULATIONS

8.1 Pregnancy

Risk Summary

There are no available data on ciprofloxacin and dexamethasone otic suspension use in pregnant women to evaluate for a drug-associated risk of major birth defects, miscarriage or adverse maternal, or fetal outcomes. Because of the minimal systemic absorption of ciprofloxacin and dexamethasone following topical otic administration of ciprofloxacin and dexamethasone otic suspension, this product is expected to be of minimal risk for maternal and fetal toxicity when administered to pregnant women [see Clinical Pharmacology (12.3)].

Animal reproduction studies have not been conducted with ciprofloxacin and dexamethasone otic suspension. Oral administration of ciprofloxacin during organogenesis at doses up to 100 mg/kg to pregnant mice and rats, and up to 30 mg/kg to pregnant rabbits did not cause fetal malformations (see Data). These doses were at least 200 times the recommended otic human dose (ROHD in mice, rats, and rabbits, respectively, based on body surface area (BSA). With dexamethasone, malformations have been observed in animal studies after ocular and systemic administration.

The estimated background risk of major birth defects and miscarriage for the indicated population is unknown. All pregnancies have a background risk of birth defect, loss, or other adverse outcomes. In the U.S. general population, the estimated background risk of major birth defects and miscarriage in clinically recognized pregnancies is 2% to 4% and of miscarriage is 15% to 20%, respectively.

Data

Animal Data

Ciprofloxacin

Developmental toxicology studies have been performed with ciprofloxacin in rats, mice, and rabbits. The doses used in these studies are, at a minimum, approximately 200 times greater than the recommended otic human dose based on body surface area. In rats and mice, oral doses up to 100 mg/kg administered during organogenesis (Gestation Days [GD], 6-17) were not associated with adverse developmental outcomes, including embryofetal toxicity or malformations. A 30 mg/kg oral dose was associated with suppression of maternal and fetal body weight gain, but fetal malformations were not observed. Intravenous administration of doses up to 20 mg/kg to pregnant rabbits was not maternally toxic and neither embryo-fetal toxicity nor fetal malformations were observed. To mitigate maternal toxicity in these studies, groups of rabbits received ciprofloxacin for a different 5 day dosing period covering organogenesis (GD 6-18).

Dexamethasone

Dexamethasone has been shown to be teratogenic in mice and rabbits following topical ophthalmic application. In a rat oral developmental toxicity study, no adverse effects were observed at 0.01 mg/kg/day (0.1 times the ROHD based on BSA), although embryotoxicity was observed at higher doses.

8.2 Lactation

Risk Summary

It is not known whether ciprofloxacin and dexamethasone are present in human milk following topical otic administration.

Published literature reports the presence of ciprofloxacin in human milk after oral administration to lactating women. However, because of the minimal systemic absorption of ciprofloxacin following topical otic administration of ciprofloxacin and dexamethasone otic suspension, breastfeeding is not expected to result in the exposure of the infant to ciprofloxacin [see Clinical Pharmacology (12.3)].

Systemically administered corticosteroids appear in human milk. Dexamethasone in breast milk could suppress growth, interfere with endogenous corticosteroid production, or cause other untoward effects. However, it is not known whether topical otic administration of ciprofloxacin or dexamethasone could result in systemic absorption that is sufficient to produce detectable quantities of dexamethasone in human milk.

There are no data on the effects of ciprofloxacin or dexamethasone on milk production.

The developmental and health benefits of breastfeeding should be considered along with the mother’s clinical need for ciprofloxacin and dexamethasone otic suspension and any potential adverse effects on the breast-fed child from ciprofloxacin and dexamethasone otic suspension.

8.4 Pediatric Use

The safety and efficacy of ciprofloxacin and dexamethasone otic suspension have been established in pediatric patients 6 months and older (937 patients) in adequate and well-controlled clinical trials.

No clinically relevant changes in hearing function were observed in 69 pediatric patients (age 4 to 12 years) treated with ciprofloxacin and dexamethasone otic suspension and tested for audiometric parameters.

10 OVERDOSAGE

Due to the characteristics of this preparation, no toxic effects are to be expected with an otic overdose of this product.

11 DESCRIPTION

Ciprofloxacin 0.3% and dexamethasone 0.1% sterile otic suspension contains the quinolone antimicrobial, ciprofloxacin hydrochloride, combined with the corticosteroid, dexamethasone, in a sterile, preserved suspension for otic use. Each mL of ciprofloxacin and dexamethasone otic suspension contains Actives: ciprofloxacin hydrochloride equivalent to 3 mg ciprofloxacin base and 1 mg dexamethasone. Preservative: 0.1 mg benzalkonium chloride. Inactives: acetic acid, boric acid, edetate disodium, hydroxyethyl cellulose, purified water, sodium acetate, sodium chloride, and tyloxapol. Sodium hydroxide or hydrochloric acid may be added for adjustment of pH.

Ciprofloxacin, a quinolone antimicrobial is available as the monohydrochloride monohydrate salt of 1-cyclopropyl-6-fluoro-1,4-dihydro-4-oxo-7-(1-piperazinyl)-3-quinoline carboxylic acid. The empirical formula is C17H18FN3O3·HCl·H2O. The molecular weight is 385.82 g/mol and the structural formula is:

Dexamethasone, 9-fluoro-11(beta),17,21-trihydroxy-16(alpha)-methylpregna-1,4-diene-3,20-dione, is a corticosteroid. The empirical formula is C22H29FO5. The molecular weight is 392.46 g/mol and the structural formula is:

12 CLINICAL PHARMACOLOGY

12.1 Mechanism of Action

Ciprofloxacin is a fluoroquinolone antibacterial [see Microbiology (12.4)].

Dexamethasone, a corticosteroid, has been shown to suppress inflammation by inhibiting multiple inflammatory cytokines resulting in decreased edema, fibrin deposition, capillary leakage, and migration of inflammatory cells.

12.3 Pharmacokinetics

Following a single bilateral 4-drop (total dose = 0.28 mL, 0.84 mg ciprofloxacin, 0.28 mg dexamethasone) topical otic dose of ciprofloxacin and dexamethasone otic suspension to pediatric patients after tympanostomy tube insertion, measurable plasma concentrations of ciprofloxacin and dexamethasone were observed at 6 hours following administration in 2 of 9 patients and 5 of 9 patients, respectively.

Mean ± SD peak plasma concentrations of ciprofloxacin were 1.39 ± 0.880 ng/mL (n = 9). Peak plasma concentrations ranged from 0.543 ng/mL to 3.45 ng/mL and were on average approximately 0.1% of peak plasma concentrations achieved with an oral dose of 250-mg. Peak plasma concentrations of ciprofloxacin were observed within 15 minutes to 2 hours post dose application.

Mean ± SD peak plasma concentrations of dexamethasone were 1.14 ± 1.54 ng/mL (n = 9). Peak plasma concentrations ranged from 0.135 ng/mL to 5.10 ng/mL and were on average approximately 14% of peak concentrations reported in the literature following an oral 0.5-mg tablet dose. Peak plasma concentrations of dexamethasone were observed within 15 minutes to 2 hours post dose application.

Dexamethasone has been added to aid in the resolution of the inflammatory response accompanying bacterial infection (such as otorrhea in pediatric patients with AOMT).

12.4 Microbiology

Mechanism of Action
The bactericidal action of ciprofloxacin results from interference with the enzyme, DNA gyrase, which is needed for the synthesis of bacterial DNA.

Resistance
Cross-resistance has been observed between ciprofloxacin and other fluoroquinolones. There is generally no cross-resistance between ciprofloxacin and other classes of anti-bacterial agents, such as beta-lactams or aminoglycosides.

Antimicrobial Activity
Ciprofloxacin has been shown to be active against most isolates of the following microorganisms, both in vitro and clinically in otic infections [see Indications and Usage (1)].

Aerobic Bacteria
Gram-positive Bacteria

- Staphylococcus aureus
- Streptococcus pneumoniae

Gram-negative Bacteria

- Haemophilus influenzae
- Moraxella catarrhalis
- Pseudomonas aeruginosa

13 NONCLINICAL TOXICOLOGY

13.1 Carcinogenesis, Mutagenesis, Impairment of Fertility

Carcinogenesis

Long-term carcinogenicity studies in mice and rats have been completed for ciprofloxacin. After daily oral doses of 750 mg/kg (mice) and 250 mg/kg (rats) were administered for up to 2 years, there was no evidence that ciprofloxacin had any carcinogenic or tumorigenic effects in these species. No long-term studies of ciprofloxacin and dexamethasone otic suspension have been performed to evaluate carcinogenic potential.

Long-term studies have not been performed to evaluate the carcinogenic potential of topical otic dexamethasone.

Mutagenesis

Eight in vitro mutagenicity tests have been conducted with ciprofloxacin, and the test results are listed below:

- Salmonella/Microsome Test (Negative)
- E. coli DNA Repair Assay (Negative)
- Mouse Lymphoma Cell Forward Mutation Assay (Positive)
- Chinese Hamster V79 Cell HGPRT Test (Negative)
- Syrian Hamster Embryo Cell Transformation Assay (Negative)
- Saccharomyces cerevisiae Point Mutation Assay (Negative)
- Saccharomyces cerevisiae Mitotic Crossover and Gene Conversion Assay (Negative)
- Rat Hepatocyte DNA Repair Assay (Positive)

Thus, 2 of the 8 tests were positive, but results of the following 3 in vivo test systems gave negative results:

- Rat Hepatocyte DNA Repair Assay
- Micronucleus Test (Mice)
- Dominant Lethal Test (Mice)

Dexamethasone has been tested for in vitro and in vivo genotoxic potential and shown to be positive in the following assays: chromosomal aberrations, sister-chromatid exchange in human lymphocytes, and micronuclei and sister-chromatid exchanges in mouse bone marrow. However, the Ames/Salmonella assay, both with and without S9 mix, did not show any increase in His+ revertants.

Impairment of Fertility

Fertility studies performed in male and female rats at oral doses of ciprofloxacin up to 100 mg/kg (approximately 482 times the ROHD of ciprofloxacin based on BSA) revealed no evidence of impairment. Male rats received oral ciprofloxacin for 10 weeks prior to mating and females were dosed for 3 weeks prior to mating through GD 7.

The effect of dexamethasone on fertility has not been investigated following topical otic application. However, the lowest toxic dose of dexamethasone identified following topical dermal application was 1.802 mg/kg in a 26-week study in male rats and resulted in changes to the testes, epididymis, sperm duct, prostate, seminal vesicle, Cowper's gland, and accessory glands. The relevance of this study for short-term topical otic use is unknown.

13.2 Animal Toxicology and/or Pharmacology

Guinea pigs dosed in the middle ear with ciprofloxacin and dexamethasone otic suspension for one month exhibited no drug-related structural or functional changes of the cochlear hair cells and no lesions in the ossicles.

14 CLINICAL STUDIES

In a randomized, multicenter, controlled clinical trial, ciprofloxacin and dexamethasone otic suspension dosed 2 times per day for 7 days demonstrated clinical cures in the per protocol analysis in 86% of AOMT patients compared to 79% for ofloxacin solution, 0.3%, dosed 2 times per day for 10 days. Among culture positive patients, clinical cures were 90% for ciprofloxacin and dexamethasone otic suspension compared to 79% for ofloxacin solution, 0.3%. Microbiological eradication rates for these patients in the same clinical trial were 91% for ciprofloxacin and dexamethasone otic suspension compared to 82% for ofloxacin solution, 0.3%.

In 2 randomized multicenter, controlled clinical trials, ciprofloxacin and dexamethasone otic suspension dosed 2 times per day for 7 days demonstrated clinical cures in 87% and 94% of per protocol evaluable AOE patients, respectively, compared to 84% and 89%, respectively, for otic suspension containing neomycin 0.35%, polymyxin B 10,000 units/mL, and hydrocortisone 1.0% (neo/poly/HC). Among culture-positive patients, clinical cures were 86% and 92% for ciprofloxacin and dexamethasone otic suspension compared to 84% and 89%, respectively, for neo/poly/HC. Microbiological eradication rates for these patients in the same clinical trials were 86% and 92% for ciprofloxacin and dexamethasone otic suspension compared to 85% and 85%, respectively, for neo/poly/HC.

16 HOW SUPPLIED/STORAGE AND HANDLING

How Supplied

Ciprofloxacin 0.3% and dexamethasone 0.1% sterile otic suspension is a white-to off-white suspension supplied as follows: 7.5 mL fill in a system consisting of a natural polyethylene bottle and natural plug, with a white polypropylene closure.

7.5 mL fill NDC 0781-6186-67

Storage
Store at 20°C to 25°C (68°F to 77°F); excursions permitted between 15°C and 30°C (59°F and 86°F) [see USP Controlled Room Temperature].
Avoid freezing. Protect from light.

17 PATIENT COUNSELING INFORMATION

Advise the patient to read the FDA-approved patient labeling (Patient Information and Instructions for Use).

For Otic Use Only

Advise patients that ciprofloxacin and dexamethasone otic suspension is for otic use (ears) only. This product must not be used in the eye [see Dosage and Administration (2.2)].

Administration Instructions

Instruct patients to warm the bottle in their hand for one to two minutes prior to use and shake well immediately before using [see Dosage and Administration (2.1, 2.2)].

Allergic Reactions

Advise patients to discontinue use immediately and contact their physician, if rash or allergic reaction occurs [see Warnings and Precautions (5.1)].

Avoid Contamination of the Product

Advise patients to avoid contaminating the tip with material from the ear, fingers, or other sources [see Instructions for Use].

Duration of Use

Advise patients that it is very important to use the eardrops for as long as their doctor has instructed, even if the symptoms improve [see Patient Information].

Protect from Light

Advise patients to protect the product from light [see How Supplied/Storage and Handling (16)].

Unused Product

Advise patients to discard unused portion after therapy is completed [see Dosage and Administration (2.2)].

Manufactured by

Novartis Manufacturing NV

Puurs-Sint-Amands, Belgium for

Sandoz Inc., Princeton, NJ 08540

PATIENT INFORMATION
CIPROFLOXACIN AND DEXAMETHASONE

(sih-proe-FLOX-ah-sin) and (dex-ah-METH-ah-sone)

OTIC SUSPENSION

What is CIPROFLOXACIN AND DEXAMETHASONE OTIC SUSPENSION?
  CIPROFLOXACIN AND DEXAMETHASONE OTIC SUSPENSION is a prescription medicine used in the ear only (otic use) that contains 2 medicines, a quinolone antibiotic medicine called ciprofloxacin and a corticosteroid medicine called dexamethasone. CIPROFLOXACIN AND DEXAMETHASONE OTIC SUSPENSION is used in adults and children 6 months of age or older to treat certain types of infections caused by certain germs called bacteria. These bacterial infections include:
2. middle ear infection (known as acute otitis media or AOM) in people who have a tube in their eardrum known as a tympanostomy to prevent having too much fluid in the middle ear
3. outer ear canal infection (known as acute otitis externa or AOE)
It is not known if CIPROFLOXACIN AND DEXAMETHASONE OTIC SUSPENSION is safe and effective in children under 6 months of age.

Who should not use CIPROFLOXACIN AND DEXAMETHASONE OTIC SUSPENSION?

Do not use CIPROFLOXACIN AND DEXAMETHASONE OTIC SUSPENSION if you:

- are allergic to ciprofloxacin, quinolones, or any of the ingredients in CIPROFLOXACIN AND DEXAMETHASONE OTIC SUSPENSION. See the end of this Patient Information leaflet for a complete list of ingredients in CIPROFLOXACIN AND DEXAMETHASONE OTIC SUSPENSION.
- have an outer ear canal infection caused by certain viruses, including the herpes simplex virus.
- have an ear infection caused by a fungus.

What should I tell my doctor before using CIPROFLOXACIN AND DEXAMETHASONE OTIC SUSPENSION?
Before using CIPROFLOXACIN AND DEXAMETHASONE OTIC SUSPENSION, tell your doctor about all of your medical conditions, including if you:

- are pregnant or plan to become pregnant. It is not known if CIPROFLOXACIN AND DEXAMETHASONE OTIC SUSPENSION will harm your unborn baby.
- are breastfeeding or plan to breastfeed. It is not known if CIPROFLOXACIN AND DEXAMETHASONE OTIC SUSPENSION passes into your breast milk. Talk to your doctor about the best way to feed your baby during treatment with CIPROFLOXACIN AND DEXAMETHASONE OTIC SUSPENSION.
Tell your doctor about all the medicines you take, including prescription and over-the-counter medicines, vitamins, and herbal supplements.

How should I use CIPROFLOXACIN AND DEXAMETHASONE OTIC SUSPENSION?

- Read the detailed Instructions for Use that come with CIPROFLOXACIN AND DEXAMETHASONE OTIC SUSPENSION.
- Use CIPROFLOXACIN AND DEXAMETHASONE OTIC SUSPENSION exactly as your doctor tells you to.
- CIPROFLOXACIN AND DEXAMETHASONE OTIC SUSPENSION is for use in the ear only (otic use). Do not use CIPROFLOXACIN AND DEXAMETHASONE OTIC SUSPENSION in the eye or inject CIPROFLOXACIN AND DEXAMETHASONE OTIC SUSPENSION.
- Apply 4 drops of CIPROFLOXACIN AND DEXAMETHASONE OTIC SUSPENSION into the affected ear 2 times a day for 7 days.
- Do not stop using CIPROFLOXACIN AND DEXAMETHASONE OTIC SUSPENSION unless your doctor tells you to, even if your symptoms improve.
If your symptoms do not improve after 7 days of treatment with CIPROFLOXACIN AND DEXAMETHASONE OTIC SUSPENSION, call your doctor.
- Call your doctor right away if:
  - you have fluid that continues to drain from your ear (otorrhea) after you have finished your treatment with CIPROFLOXACIN AND DEXAMETHASONE OTIC SUSPENSION
  - you have fluid that drains from your ear 2 or more times within 6 months after you stop treatment with CIPROFLOXACIN AND DEXAMETHASONE OTIC SUSPENSION

What are the possible side effects of CIPROFLOXACIN AND DEXAMETHASONE OTIC SUSPENSION?
CIPROFLOXACIN AND DEXAMETHASONE OTIC SUSPENSION may cause serious side effects, including:

- allergic reactions. Stop using CIPROFLOXACIN AND DEXAMETHASONE OTIC SUSPENSION and call your doctor or go to the nearest emergency room if you have any of the following signs or symptoms of an allergic reaction:

o hives (urticaria)

o trouble breathing

o swelling of your face, lips, mouth, or tongue

o dizziness, fast heartbeat, or pounding in your chest

o rash

o itching

The most common side effects of CIPROFLOXACIN AND DEXAMETHASONE OTIC SUSPENSION include:

- ear discomfort
- ear pain
- ear itching (pruritus)
These are not all the possible side effects of CIPROFLOXACIN AND DEXAMETHASONE OTIC SUSPENSION. Call your doctor for medical advice about side effects. You may report side effects to FDA at 1-800-FDA-1088.

How should I store CIPROFLOXACIN AND DEXAMETHASONE OTIC SUSPENSION?

- Store at 20°C to 25°C (68°F to 77°F); excursions permitted between 15°C and 30°C (59°F and 86°F) [see USP Controlled Room Temperature].
- Do not freeze CIPROFLOXACIN AND DEXAMETHASONE OTIC SUSPENSION.
- Keep CIPROFLOXACIN AND DEXAMETHASONE OTIC SUSPENSION out of light.

Keep CIPROFLOXACIN AND DEXAMETHASONE OTIC SUSPENSION and all medicines out of the reach of children.

General information about the safe and effective use of CIPROFLOXACIN AND DEXAMETHASONE OTIC SUSPENSION.
Medicines are sometimes prescribed for purposes other than those listed in a Patient Information leaflet. Do not use CIPROFLOXACIN AND DEXAMETHASONE OTIC SUSPENSION for a condition for which it was not prescribed. Do not give CIPROFLOXACIN AND DEXAMETHASONE OTIC SUSPENSION to other people, even if they have the same symptoms that you have. It may harm them. You can ask your pharmacist or doctor for information about CIPROFLOXACIN AND DEXAMETHASONE OTIC SUSPENSION that is written for health professionals.

What are the ingredients in CIPROFLOXACIN AND DEXAMETHASONE OTIC SUSPENSION?
Actives: ciprofloxacin hydrochloride equivalent to 3 mg ciprofloxacin base and 1 mg dexamethasone. Preservative: 0.1 mg benzalkonium chloride.
Inactives: acetic acid, boric acid, edetate disodium, hydroxyethyl cellulose, purified water, sodium acetate, sodium chloride, and tyloxapol. Sodium hydroxide or hydrochloric acid may be added for adjustment of pH.
Manufactured by

Novartis Manufacturing NV

Puurs-Sint-Amands, Belgium for

Sandoz Inc., Princeton, NJ 08540

This Patient Information has been approved by the U.S. Food and Drug Administration. Revised:01/2025

INSTRUCTIONS FOR USE
CIPROFLOXACIN AND DEXAMETHASONE

(sih-proe-FLOX-ah-sin) and (dex-ah-METH-ah-sone)

OTIC SUSPENSION

This “Instructions for Use” contains information on how to use CIPROFLOXACIN AND DEXAMETHASONE OTIC SUSPENSION.

Important Information You Need to Know Before Using CIPROFLOXACIN AND DEXAMETHASONE OTIC SUSPENSION.
Read this Instructions for Use that comes with CIPROFLOXACIN AND DEXAMETHASONE OTIC SUSPENSION before you start using it and each time you get a refill. There may be new information. This information does not take the place of talking with your doctor about your medical condition or treatment.

- Use CIPROFLOXACIN AND DEXAMETHASONE OTIC SUSPENSION exactly as your doctor tells you to use it.
- CIPROFLOXACIN AND DEXAMETHASONE OTIC SUSPENSION is for use in the ear only (otic use). Do not inject CIPROFLOXACIN AND DEXAMETHASONE OTIC SUSPENSION or use CIPROFLOXACIN AND DEXAMETHASONE OTIC SUSPENSION in the eye.
- Shake CIPROFLOXACIN AND DEXAMETHASONE OTIC SUSPENSION well before each use.
- Do not touch your ear, fingers, or other surfaces with the tip of the CIPROFLOXACIN AND DEXAMETHASONE OTIC SUSPENSION bottle. You may get bacteria on the tip of the bottle that can cause you to get another infection.

How should I use CIPROFLOXACIN AND DEXAMETHASONE OTIC SUSPENSION?

Step 1. Wash your hands with soap and water (see Figure A).

Figure A

Step 2. Warm the bottle of CIPROFLOXACIN AND DEXAMETHASONE OTIC SUSPENSION by rolling the bottle between your hands for 1 to 2 minutes (see Figure B). Shake the bottle of CIPROFLOXACIN AND DEXAMETHASONE OTIC SUSPENSION well.

Figure B

Step 3. Remove the CIPROFLOXACIN AND DEXAMETHASONE OTIC SUSPENSION cap. Put the cap in a clean and dry area. Do not let the tip of the bottle touch your ear, fingers or other surfaces.

Step 4. Lie down on your side so that the affected ear faces upward (see Figure C).

Figure C

Step 5. Hold the bottle of CIPROFLOXACIN AND DEXAMETHASONE OTIC SUSPENSION between your thumb and index finger (see Figure D). Place the tip of the bottle close to your ear. Be careful not to touch your fingers or ear with the tip of the bottle.

Figure D

Step 6. Gently squeeze the bottle and let 4 drops of CIPROFLOXACIN AND DEXAMETHASONE OTIC SUSPENSION fall into the affected ear. If a drop misses your ear, follow the instructions in Step 5 again.

Step 7. Stay on your side with the affected ear facing upward (see Figure C).

It is important that you follow the instructions below for your specific ear infection, to allow CIPROFLOXACIN AND DEXAMETHASONE OTIC SUSPENSION to enter the affected part of your ear.

Step 8.

If you use CIPROFLOXACIN AND DEXAMETHASONE OTIC SUSPENSION to treat a middle ear infection, and you have a tube in your eardrum known as a tympanostomy:

- Gently press the part of the ear known as the tragus (see Figure E) 5 times using a pumping motion (see Figure E). This will allow the drops of CIPROFLOXACIN AND DEXAMETHASONE OTIC SUSPENSION to enter your middle ear.
- Remain on your side with the affected ear facing upward (see Figure C) for 1 minute.

Figure E

If you use CIPROFLOXACIN AND DEXAMETHASONE OTIC SUSPENSION to treat an outer ear canal infection:

- Gently pull the outer ear lobe upward and backward (see Figure F). This will allow the drops of CIPROFLOXACIN AND DEXAMETHASONE OTIC SUSPENSION to enter your ear canal.
- Remain on your side with the affected ear facing upward (see Figure C) for 1 minute.

Figure F

Step 9. If your doctor has told you to use CIPROFLOXACIN AND DEXAMETHASONE OTIC SUSPENSION in both ears, repeat steps 5-8 for your other ear.

Step 10. Put the cap back on the bottle and close it tightly.

Step 11. After you have used all of your CIPROFLOXACIN AND DEXAMETHASONE OTIC SUSPENSION doses, there may be some CIPROFLOXACIN AND DEXAMETHASONE OTIC SUSPENSION left in the bottle. Throw the bottle away.

How should I store CIPROFLOXACIN AND DEXAMETHASONE OTIC SUSPENSION?

- Store at 20°C to 25°C (68°F to 77°F); excursions permitted between 15°C and 30°C (59°F and 86°F) [see USP Controlled Room Temperature].
- Do not freeze CIPROFLOXACIN AND DEXAMETHASONE OTIC SUSPENSION.
- Keep CIPROFLOXACIN AND DEXAMETHASONE OTIC SUSPENSION out of light.

Keep CIPROFLOXACIN AND DEXAMETHASONE OTIC SUSPENSION and all medicines out of the reach of children.

If you would like more information, talk with your doctor. You can ask your pharmacist or doctor for more information about CIPROFLOXACIN AND DEXAMETHASONE OTIC SUSPENSION that is written for health professionals.

Manufactured by

Novartis Manufacturing NV

Puurs-Sint-Amands, Belgium for

Sandoz Inc., Princeton, NJ 08540

This Instructions for Use has been approved by the U.S. Food and Drug Administration. Revised: 01/2025

9107830 US

PRINCIPAL DISPLAY PANEL

NDC 0781-6186-67 Rx Only

Ciprofloxacin 0.3%

and

Dexamethasone 0.1%

Otic Suspension

FOR USE IN EARS ONLY

STERILE

7.5 ml

SANDOZ